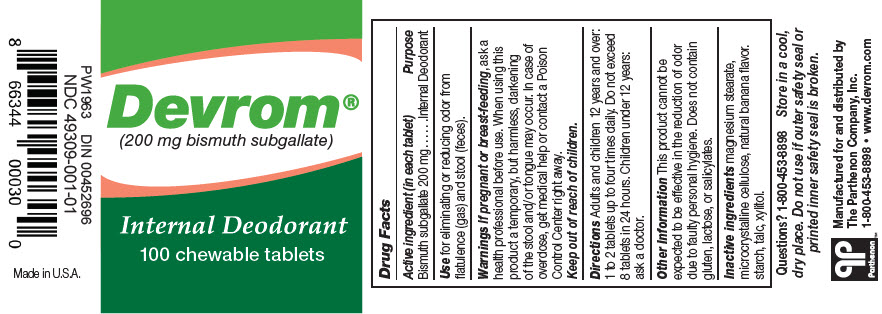 DRUG LABEL: Devrom
NDC: 49309-001 | Form: TABLET, CHEWABLE
Manufacturer: The Parthenon Co., Inc.
Category: otc | Type: HUMAN OTC DRUG LABEL
Date: 20241112

ACTIVE INGREDIENTS: BISMUTH SUBGALLATE 200 mg/1 1
INACTIVE INGREDIENTS: MAGNESIUM STEARATE; MICROCRYSTALLINE CELLULOSE; STARCH, CORN; TALC; XYLITOL

Devrom®

Drug Facts

Active ingredient (in each tablet)

Bismuth subgallate 200 mg

Purpose

Internal Deodorant

Use

for eliminating or reducing odor from flatulence (gas) and stool (feces).

Warnings

If pregnant or breast-feeding, ask a health professional before use. When using this product a temporary, but harmless, darkening of the stool and/or tongue may occur. In case of overdose, get medical help or contact a Poison Control Center right away.

Keep out of reach of children.

Directions

Adults and children 12 years and over: 1 to 2 tablets up to four times daily. Do not exceed 8 tablets in 24 hours. Children under 12 years: ask a doctor.

Other Information

This product cannot be expected to be effective in the reduction of odor due to faulty personal hygiene. Does not contain gluten, lactose, or salicylates.

Inactive ingredients

magnesium stearate, microcrystalline cellulose, natural banana flavor. starch, talc, xylitol.

Questions?

1-800-453-8898

distributed by
The Parthenon Company, Inc.

PRINCIPAL DISPLAY PANEL - 100 Tablet Bottle Label

Devrom®
(200 mg bismuth subgallate)

Internal Deodarant
100 chewable tablets